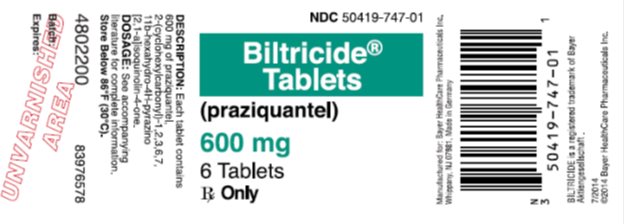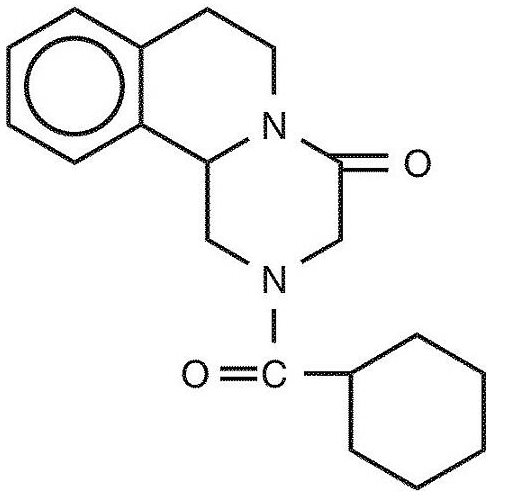 DRUG LABEL: Biltricide
NDC: 50419-747 | Form: TABLET, FILM COATED
Manufacturer: Bayer HealthCare Pharmaceuticals Inc.
Category: prescription | Type: HUMAN PRESCRIPTION DRUG LABEL
Date: 20231206

ACTIVE INGREDIENTS: PRAZIQUANTEL 600 mg/1 1
INACTIVE INGREDIENTS: STARCH, CORN; MAGNESIUM STEARATE; MICROCRYSTALLINE CELLULOSE; CROSPOVIDONE, UNSPECIFIED; SODIUM LAURYL SULFATE; POLYETHYLENE GLYCOL, UNSPECIFIED; TITANIUM DIOXIDE; HYPROMELLOSE, UNSPECIFIED

HIGHLIGHTS OF PRESCRIBING INFORMATION

These highlights do not include all the information needed to use BILTRICIDE safely and effectively. See full prescribing information for BILTRICIDE.
BILTRICIDE (praziquantel) tablets, for oral use
Initial U.S. Approval: 1982

RECENT MAJOR CHANGES

Warnings and Precautions (5.6) 12/2023

1 INDICATIONS AND USAGE

Biltricide is an anthelmintic indicated in patients aged one year and older for the treatment of the following infections:

- Schistosomiasis due to all species of schistosoma (for example, Schistosoma mekongi, Schistosoma japonicum, Schistosoma mansoni and Schistosoma hematobium), and,
- Clonorchiasis and Opisthorchiasis due to the liver flukes, Clonorchis sinensis and Opisthorchis viverrini

2 DOSAGE AND ADMINISTRATION

- Schistosomiasis: 20 mg/kg bodyweight 3 times a day separated by 4 to 6 hours for 1 day only. (2.1)
- Clonorchiasis and Opisthorchiasis: 2 5 mg/kg 3 times a day separated by 4 to 6 hours for 1 day only. (2.1)
- Take with water during meals. Do not chew or keep segments in the mouth. (2.2)
- For pediatric patients under 6 years of age, the tablets may be crushed or disintegrated and mixed with semi-solid food or liquid. (2.2)
- For additional administration instructions see the full prescribing information.

3 DOSAGE FORMS AND STRENGTHS

- Tablets: 600 mg (with three scores (notches) on the tablet) (3)

4 CONTRAINDICATIONS

- Known hypersensitivity to Biltricide or any of its ingredients. (4.1)
- Concomitant administration with strong Cytochrome P450 3A enzyme (CYP 3A) inducers such as rifampin. (4, 5.6 7.1)

5 WARNINGS AND PRECAUTIONS

- Clinical Deterioration: Potentially life threatening clinical deterioration can occur in patients treated during the acute phase of schistosomiasis. (5.1)
- Central Nervous System (CNS) Effects: Biltricide can exacerbate central nervous system pathology due to schistosomiasis. Consider whether to administer to individuals reporting a history of epilepsy and/or other signs of potential central nervous systems involvement such as subcutaneous nodules suggestive of cysticercosis. (5.2)
- Potential Lack of Efficacy for Acute Schistosomiasis: This has been reported in observational studies (5.3).
- Cardiac Arrhythmias: Bradycardia, ectopic rhythms, ventricular fibrillation, and AV blocks has been observed with Biltricide administration. Monitor patients with cardiac arrhythmias during treatment (5.4).

6 ADVERSE REACTIONS

The adverse reactions reported were malaise, headache, dizziness, abdominal discomfort (with or without nausea), pyrexia and urticaria. (6)

To report SUSPECTED ADVERSE REACTIONS, contact Bayer HealthCare Pharmaceuticals Inc. at 1-888-842-2937 or FDA at 1-800-FDA-1088 or www.fda.gov/medwatch.

7 DRUG INTERACTIONS

Moderate CYP 3A Inducers: Avoid concomitant administration of moderate CYP 3A inducers, for example, efavirenz (5.6, 7.1)

8 USE IN SPECIFIC POPULATIONS

- Pediatrics: Safety has not been established in pediatric patients younger than 1 year of age. (8.4)
- Hepatic Impairment: Monitor patients for adverse reactions when administering the recommended dose of Biltricide to hepatosplenic schistosomiasis patients with moderate to severe liver impairment (Child-Pugh Class B or C). (8.6)

FULL PRESCRIBING INFORMATION

1 INDICATIONS AND USAGE

Biltricide is indicated in patients aged 1 year and older for the treatment of the following infections:

- Schistosomiasis due to all species of schistosoma (for example, Schistosoma mekongi, Schistosoma japonicum, Schistosoma mansoni and Schistosoma hematobium), and
- Clonorchiasis and Opisthorchiasis due to the liver flukes, Clonorchis sinensis/Opisthorchis viverrini (approval of this indication was based on studies in which the two species were not differentiated)

2 DOSAGE AND ADMINISTRATION

2.1 Recommended Dosage

Schistosomiasis The recommended dosage for the treatment of schistosomiasis is 20 mg/kg bodyweight administered orally three times a day separated by 4 to 6 hours, for 1 day only.

Clonorchiasis and Opisthorchiasis

The recommended dosage for the treatment of clonorchiasis and opisthorchiasis is 25 mg/kg bodyweight administered orally three times a day separated by 4 to 6 hours for 1 day only.

2.2 Administration

Take tablets with water during meals. Do not chew or keep the tablets (or parts of tablets) in the mouth; the bitter taste may cause gagging or vomiting. To prevent choking in pediatric patients under 6 years of age, the tablets may be crushed or disintegrated and mixed with semi-solid food or liquid. Use crushed or disintegrated tablets within 1 hour of mixing.

Biltricide 600 mg tablets have three scores which can be split into four segments at the scores. When broken, each of the four segments contains 150 mg of praziquantel so that the dosage can be adjusted to the patient’s bodyweight. Segments are broken off by pressing the score (notch) with thumbnails. If one-quarter of a tablet is required, this is best achieved by breaking the segment from the outer end.

3 DOSAGE FORMS AND STRENGTHS

Biltricide tablets contain 600 mg of praziquantel. The tablets are white to orange tinged, film-coated, oblong with three scores (notches), imprinted with “BAYER” on one side and “LG” on the other side.

4 CONTRAINDICATIONS

Biltricide is contraindicated in:

- Patients who previously have shown hypersensitivity to praziquantel or any of the excipients in Biltricide.
- Patients with ocular cysticercosis; since parasite destruction within the eye that occurs because of hypersensitivity reaction to the dead parasite after treatment may cause irreversible lesions, ocular cysticercosis must not be treated with Biltricide.
- Patients taking strong Cytochrome P450 3A enzyme (CYP3A) inducers, such as rifampin, [see Warnings and Precautions (5.6) and Drug Interactions (7.1, 7.2)].

5 WARNINGS AND PRECAUTIONS

5.1 Clinical Deterioration

The use of Biltricide in patients with schistosomiasis may be associated with clinical deterioration (for example, paradoxical reactions, serum sickness Jarisch-Herxheimer like reactions: sudden inflammatory immune response suspected to be caused by the release of schistosomal antigens). These reactions predominantly occur in patients treated during the acute phase of schistosomiasis. They may lead to potentially life-threatening events, for example, respiratory failure, encephalopathy, papilledema, and/or cerebral vasculitis.

5.2 Central Nervous System (CNS) Effects

Biltricide can exacerbate central nervous system pathology due to schistosomiasis, paragonimiasis, or Taenia solium cysticercosis. As a general rule, consider whether to administer Biltricide to individuals reporting a history of epilepsy and/or other signs of potential central nervous systems involvement such as subcutaneous nodules suggestive of cysticercosis unless the potential benefit justifies the potential risk. Hospitalize the patient for duration of treatment when schistosomiasis or fluke infection is found to be associated with cerebral cysticercosis.

5.3 Potential Lack of Efficacy During the Acute Phase of Schistosomiasis

Data from two observational cohort studies in patients indicate that treatment with Biltricide in the acute phase of infection may not prevent progression from asymptomatic infection to acute schistosomiasis, or from asymptomatic infection/acute schistosomiasis into chronic phase.

5.4 Cardiac Arrhythmias

Bradycardia, ectopic rhythms, ventricular fibrillation, and AV blocks has been observed with Biltricide administration. Monitor patients with cardiac arrhythmias during treatment.

5.5 Hepatic Impairment in Hepatosplenic Schistosomiasis Patients

Reduced hepatic metabolism of praziquantel results in higher and sustained plasma concentrations of unmetabolized praziquantel in patients with liver impairment [see Clinical Pharmacology (12.3)]. Monitor patients for adverse reactions when administering the recommended dose of Biltricide to hepatosplenic schistosomiasis patients with moderate or severe liver impairment (Child-Pugh Class B or C).

5.6 Concomitant Administration with Cytochrome P450 Enzyme Inducers

Strong Cytochrome P450 3A Enzyme (CYP 3A) Inducers

Concomitant administration of strong CYP 3A inducers, such as rifampin, with Biltricide is contraindicated since therapeutically effective levels of praziquantel are unlikely to be achieved. [see Contraindications (4), Drug Interactions (7.1), and Clinical Pharmacology (12.3)].

Moderate CYP 3A Inducers

Avoid concomitant administration of Biltricide with moderate CYP 3A inducers, such as efavirenz, due to risk of a clinically significant decrease in praziquantel plasma concentrations which may lead to reduced therapeutic effect of Biltricide [see Drug Interactions (7.1)].

In patients receiving a clinically significant CYP 3A inducer drug who need immediate treatment for schistosomiasis, alternative agents for schistosomiasis should be considered, where possible. If Biltricide is necessary immediately, increase monitoring for reduced anthelmintic efficacy associated with Biltricide [see Drug Interactions (7.1)].

In patients receiving a clinically significant CYP 3A inducer drug whose treatment could be delayed, discontinue the CYP 3A inducer drug at least 2 weeks to 4 weeks before administration of Biltricide and, where possible, consider starting alternative medications that are not CYP 3A inducers. The CYP 3A inducer drug can be restarted one day after completion of Biltricide treatment, if needed [see Drug Interactions (7.1)].

6 ADVERSE REACTIONS

The following serious or otherwise important adverse reactions are discussed elsewhere in the labeling:

- Clinical Deterioration [see Warnings and Precautions (5.1)]
- Central Nervous System (CNS) Effects [see Warnings and Precautions (5.2)]
- Potential Lack of Efficacy During the Acute Phase of Schistosomiasis [see Warnings and Precautions (5.3)]
- Cardiac Arrhythmias [see Warnings and Precautions (5.4)]
- Hepatic Impairment in Hepatosplenic Schistosomiasis Patients [see Warnings and Precautions (5.5)]
- Concomitant Administration with Strong Cytochrome P450 Inducers [see Warnings and Precautions (5.6)]

The following adverse reactions associated with the use of Biltricide were identified in clinical studies, published literature or postmarketing reports. Because some of these reactions were reported voluntarily from a population of uncertain size, it is not always possible to reliably estimate their frequency or establish a causal relationship to drug exposure.

The following adverse reactions were observed in both adults and pediatric patients:

General disorders and administration site conditions: malaise, pyrexia

Nervous system disorders: headache, dizziness

Gastrointestinal disorders: abdominal discomfort, nausea

Skin and subcutaneous tissue disorders: urticaria

Such adverse reactions may be more frequent and/or serious in patients with a heavy worm burden.

Additional adverse reactions reported from worldwide post marketing experience and from publications with Biltricide and various formulations of praziquantel include:

Blood and lymphatic system disorders: eosinophilia

Cardiac disorders: arrhythmia (including bradycardia, ectopic rhythms, ventricular fibrillation, AV blocks)

Ear and labyrinth disorders: vertigo, tinnitus

Eye disorders: visual disturbance

Gastrointestinal disorders: abdominal pain, bloody diarrhea, vomiting

General disorders and administration site conditions: polyserositis, asthenia, fatigue, gait disturbance

Hepatobiliary disorders: hepatitis

Immune system disorders: allergic reaction, generalized hypersensitivity, anaphylactic reaction

Metabolism and nutrition disorders: anorexia

Musculoskeletal and connective tissue disorders: myalgia

Nervous system disorders: convulsion, somnolence, intention tremor

Respiratory, thoracic and mediastinal disorders: pneumonitis, dyspnea, wheezing

Skin and subcutaneous tissue disorders: pruritus, rash, Stevens-Johnson syndrome

Pediatric patients 1 to 17 years of age treated with Biltricide and various formulations of praziquantel experienced similar adverse reactions as those observed in adult patients.

7 DRUG INTERACTIONS

7.1 CYP 3A Inducers

Strong and Moderate CYP 3A Inducers

Concomitant administration of Biltricide with Strong and Moderate CYP 3A inducers decrease praziquantel AUC and Cmax [see Clinical Pharmacology (12.3)] which may reduce the efficacy of Biltricide. Concomitant administration of a Strong CYP 3A inducer, such as rifampin, with Biltricide is contraindicated [see Contraindications (4)]. Concomitant administration of a Moderate CYP 3A inducer, such as efavirenz, should be avoided unless the benefit outweighs the risks [see Warnings and Precautions (5.6) and Clinical Pharmacology (12.3).]

7.2 CYP450 inhibitors

Concomitant administration of drugs that decrease the activity of drug metabolizing liver enzymes (CYP450 inhibitors), for example, cimetidine, ketoconazole, itraconazole, erythromycin, and ritonavir may increase plasma concentrations of praziquantel. In addition, grapefruit juice was also reported to produce a 1.6-fold increase in the Cmax and a 1.9-fold increase in the AUC of praziquantel. The effect of this exposure increase on the safety of Biltricide has not been systematically evaluated [see Dosage and Administration (2.2)].

8.1 Pregnancy

Risk Summary

Published studies have not identified an association with Biltricide use during pregnancy and major birth defects, miscarriage or adverse maternal or fetal outcomes (see Data). In animal reproduction studies conducted in pregnant rats and rabbits no adverse developmental outcomes were observed with oral administration of praziquantel during organogenesis at approximately 0.65 times (rats) or 1.3 times (rabbits) the highest recommended human daily dose of 75 mg/kg/day, based on body surface area.

The estimated background risk of major birth defects and miscarriage for the indicated population are unknown. All pregnancies have a background risk of birth defect, loss, or other adverse outcomes. In the U.S. general population, the estimated background risk of major birth defects and miscarriage in clinically recognized pregnancies is 2 to 4% and 15 to 20%, respectively.

Data

Human Data

Two randomized controlled clinical trials have been conducted using praziquantel for the treatment of schistosoma infection in pregnant women. In one randomized controlled trial in pregnant women with schistosoma (S. japonicum) infection, 186 pregnant women were treated with praziquantel compared to 184 women who received placebo. Treatment with praziquantel during pregnancy had no effect on birthweight, and there were no differences in rates of miscarriage, fetal death and major birth defects between the praziquantel-treated and control patients. In another randomized controlled trial that included 2507 pregnant women in Uganda, 18% of women were infected with schistosoma infection. Treatment with praziquantel during pregnancy had no effect on mean birth weight, perinatal mortality or major birth defects.

In other published studies, including a retrospective observational study, case series and case reports, there have been no reports of major birth defects, stillbirths or other adverse pregnancy outcomes associated with the use of praziquantel during pregnancy.

Animal Data

No evidence of fetal harm was observed in rats and rabbits at praziquantel dose levels of 30 to 300 mg/kg body weight given repeatedly by oral administration during the period of organogenesis. These doses were up to 0.65 times (rats) or 1.3 times (rabbits) the highest recommended human daily dose of 75 mg/kg/day, based on body surface area.

8.2 Lactation

Risk Summary

Limited data from published literature reports the presence of praziquantel in human milk at low concentrations. There is no information on the effects of praziquantel in the breastfed infant or effects on milk production. The developmental and health benefits of breastfeeding should be considered along with the mother’s clinical need for Biltricide and any potential adverse effects on the breastfed infant from Biltricide or from the underlying maternal condition.

8.4 Pediatric Use

Safety and dosing recommendations of Biltricide in pediatric patients 1 to 17 years have been established. Safety of Biltricide in pediatric patients younger than 1 year of age has not been established.

Post-marketing experience and published literature indicates that pediatric patients 1 to 17 years of age treated with praziquantel experience similar adverse reactions as adults treated with praziquantel [see Adverse Reactions (6)].

8.5 Geriatric Use

Clinical studies of Biltricide did not include a sufficient number of subjects ages 65 and over to determine whether they respond differently from younger subjects. Other reported clinical experience has not identified differences in responses between the elderly and younger patients, but greater sensitivity of some older patients cannot be ruled out. This drug is known to be substantially excreted by the kidney. Because elderly patients are more likely to have decreased renal function, the risk of toxic reactions to this drug may be greater in these patients [see Clinical Pharmacology (12.3)].

8.6 Hepatic Impairment

Following oral administration of Biltricide to patients with liver impairment, reduced hepatic metabolism of praziquantel results in higher and sustained plasma concentrations of unmetabolized praziquantel [see Clinical Pharmacology (12.3)]. Monitor patients for adverse reactions when administering the recommended dose of Biltricide to hepatosplenic schistosomiasis patients with moderate or severe liver impairment (Child-Pugh Class B or C).

8.7 Renal Impairment

No dosage adjustment of Biltricide is necessary in patients with renal impairment. Nephrotoxic effects of Biltricide or its metabolites are not known [see Clinical Pharmacology (12.3)].

11 DESCRIPTION

Biltricide (praziquantel) is an anthelmintic, trematodicide provided in tablet form for oral administration.

Praziquantel is 2-(cyclohexylcarbonyl)-1,2,3,6,7, 11b-hexahydro-4H-pyrazino [2, 1-a] isoquinolin-4-one with the molecular formula; C19H24N2O2. The structural formula is as follows:

Praziquantel is a white to nearly white crystalline powder of bitter taste. The compound is stable under normal conditions and melts at 136 to 140°C with decomposition. The active substance is hygroscopic. Praziquantel is easily soluble in chloroform and dimethylsulfoxide, soluble in ethanol and very slightly soluble in water.

Biltricide tablets contain 600 mg of praziquantel. Inactive ingredients: corn starch, hypromellose, magnesium stearate, microcrystalline cellulose, polyethylene glycol, povidone, sodium lauryl sulfate, and titanium dioxide .

12 CLINICAL PHARMACOLOGY

12.1 Mechanism of Action

Praziquantel is an anthelmintic drug [see Microbiology (12.4)].

12.3 Pharmacokinetics

Absorption

After oral administration, 80% of an administered Biltricide dose is absorbed, with maximal serum concentrations of praziquantel achieved 1 to 3 hours after dosing.

Elimination

Following oral administration of Biltricide, the elimination half-life of praziquantel in serum ranges between 0.8 to 1.5 hours.

Metabolism

Praziquantel is rapidly metabolized by the cytochrome P450 enzyme system and undergoes a first pass effect after oral administration of Biltricide.

Excretion

Approximately 80% of an oral dose of Biltricide is excreted in the kidneys, almost exclusively (greater than 99%) in the form of praziquantel metabolites.

Specific Populations

Patients with Hepatic Impairment

The pharmacokinetics of praziquantel were studied in 40 patients with Schistosoma mansoni infections with varying degrees of hepatic impairment (See Table 1). In patients with schistosomiasis, the pharmacokinetic parameters did not differ significantly between those with normal hepatic function (Group 1) and those with mild (Child-Pugh class A) hepatic impairment. However, in patients with moderate-to-severe hepatic impairment (Child-Pugh class B and C), praziquantel half-life, Cmax, and AUC increased progressively with the degree of hepatic impairment. In Child-Pugh class B, the increases in mean half-life, Cmax, and AUC relative to Group 1 were 1.58-fold, 1.76-fold, and 3.55-fold, respectively. The corresponding increases in Child-Pugh class C patients were 2.82-fold, 4.29-fold, and 15-fold for half-life, Cmax, and AUC.

Table 1: Pharmacokinetic parameters of praziquantel in four groups of patients with varying degrees of liver function following administration of 40 mg/kg of Biltricide under fasting conditions.

Patient Group | Half-life; (hr) | Tmax; (hr) | Cmax; (µg/mL) | AUC; (µg/mL* hr)
Normal hepatic function (Group 1) | 2.99 ± 1.28 | 1.48 ± 0.74 | 0.83 ± 0.52 | 3.02 ± 0.59
Child-Pugh A (Group 2) | 4.66 ± 2.77 | 1.37 ± 0.61 | 0.93 ± 0.58 | 3.87 ± 2.44
Child-Pugh B (Group 3) | 4.74 ± 2.16a | 2.21 ± 0.78a,b | 1.47 ± 0.74a,b | 10.72 ± 5.53a,b
Child-Pugh C (Group 4) | 8.45 ± 2.62a,b,c | 3.2 ± 1.05a,b,c | 3.57 ± 1.30a,b,c | 45.35 ± 17.50a,b,c

a) p<0.05 compared to Group 1

b) p<0.05 compared to Group 2

c) p<0.05 compared to Group 3

Patients with Renal Impairment

Excretion of praziquantel following oral administration of Biltricide might be delayed in patients with impaired renal function, but accumulation of unchanged drug would not be expected.

Drug Interaction Studies

Rifampin (Strong CYP 3A Inducer)

In a crossover study with a 2-week washout period, 10 healthy subjects ingested a single 40 mg/kg oral dose of Biltricide following pre-treatment with oral rifampin (600 mg daily for 5 days). Plasma praziquantel concentrations were undetectable in 7 out of 10 subjects. When a single 40 mg/kg oral dose of Biltricide was administered to these same healthy subjects two weeks after discontinuation of rifampin, the mean praziquantel AUC and Cmax were 23% and 35% lower, respectively, than when Biltricide was given alone.

Efavirenz (Moderate CYP 3A Inducer)

In a crossover study, 20 healthy subjects ingested a single 40 mg/kg oral dose of Biltricide following pre-treatment with oral efavirenz (400 mg daily for 13 days). Oral efavirenz reduced the mean praziquantel AUC and Cmax by 77% (95% confidence interval: 38% to 91%) and 79% (95% confidence interval: 41% to 92%), respectively, when coadministered with Biltricide compared to Biltricide given alone.

12.4 Microbiology

Praziquantel induces a rapid contraction of schistosomes by a specific effect on the permeability of the cell membrane. The drug further causes vacuolization and disintegration of the schistosome tegument. However, the mechanism of action is unknown.

Praziquantel is active against schistosoma (for example, Schistosoma mekongi, Schistosoma japonicum, Schistosoma mansoni and Schistosoma hematobium), and infections due to the liver flukes, Clonorchis sinensis/Opisthorchis viverrini [see Indications and Usage (1)]. Published in vitro data have shown a potential lack of efficacy of praziquantel against migrating schistosomulae [see Warnings and Precautions (5.3)].

13 NONCLINICAL TOXICOLOGY

13.1 Carcinogenesis, Mutagenesis, Impairment of Fertility

Mutagenicity studies of praziquantel published in the scientific literature are inconclusive. Long term oral carcinogenicity studies in rats and golden hamsters did not reveal any carcinogenic effect at doses up to 250 mg/kg/day (about half of the human daily dose based on body surface area). Praziquantel had no effect on fertility and general reproductive performance of male and female rats when given at oral doses ranging from 30 to 300 mg/kg body weight (up to 0.65 times the human daily dose based on body surface area).

16 HOW SUPPLIED/STORAGE AND HANDLING

Biltricide is supplied as 600 mg tablets containing praziquantel. The tablets are white to orange tinged, film-coated, oblong tablets with three scores. The tablet is coded with “BAYER” on one side and “LG” on the reverse side.

Biltricide is available in bottles of six 600 mg tablets, NDC 50419-747-01.

Store below 86°F (30°C).

17 PATIENT COUNSELING INFORMATION

- Advise patients to take Biltricide during meals as directed [see Dosage and Administration (2.2)].
- Advise patients not to chew tablets and to take them with water [see Dosage and Administration (2.2)]
- Advise patients that tablets may be crushed or disintegrated and mixed with semi-solid food or liquid or disintegrated to prevent choking in children under 6 years of age. Crushed or disintegrated tablets should be used within 1 hour of mixing [see Dosage and Administration (2.2)].
- Advise patients not to take Biltricide if they are allergic to Biltricide or any of its components [see Contraindications (4)].
- Advise patients not to take Biltricide if they are taking rifampin [see Contraindications (4), Warnings and Precautions (5.6), and Drug Interactions (7.1)].
- Advise patients not to take Biltricide if they are taking efavirenz [see Warnings and Precautions (5.6), Drug Interactions (7.1)].
- Advise patients that the use of praziquantel can be associated with clinical deterioration during the acute phase of schistosomiasis [see Warnings and Precautions (5.1)].
- Advise patients that Biltricide should not be used if they have epilepsy of or other CNS effects [see Warnings and Precautions (5.2)].
- Advise patients to report any cardiac irregularities to their healthcare provider [see Warnings and Precautions (5.4)].
- Advise patients not to drive a car and not to operate machinery on the day of Biltricide treatment and the following day.

Manufactured for:

Bayer HealthCare Pharmaceuticals Inc.

Whippany, NJ 07981 USA

© 2018 Bayer HealthCare Pharmaceuticals Inc.

PACKAGE/LABEL PRINCIPAL DISPLAY PANEL

Biltricide 600 mg Tablets Bottle Label

8339661 NDC 50419-747-01

Biltricide®

Tablets

(praziquantel)

600 mg

6 Tablets

Rx Only